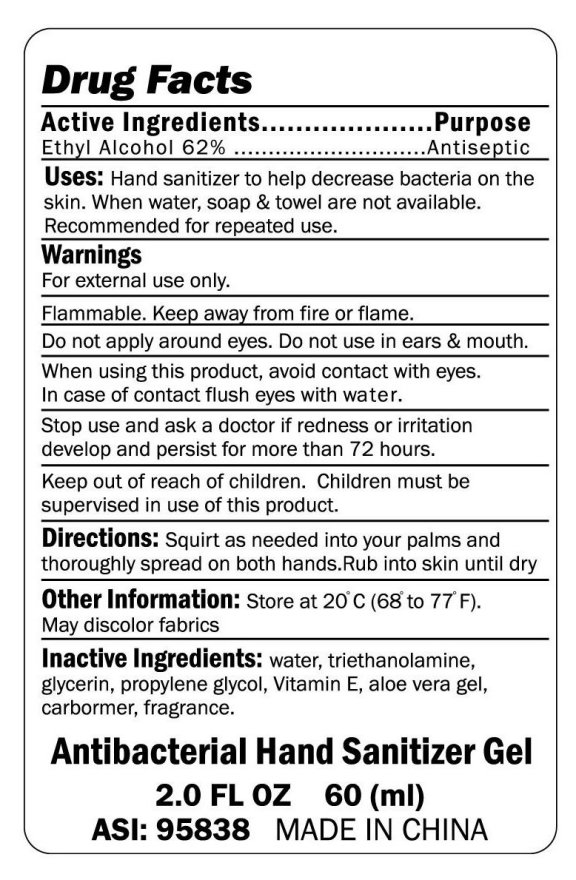 DRUG LABEL: Antibacterial Hand Sanitizer Gel
NDC: 49701-3000 | Form: GEL
Manufacturer: The Webb Company 
Category: otc | Type: HUMAN OTC DRUG LABEL
Date: 20091117

ACTIVE INGREDIENTS: ALCOHOL 62 mL/100 mL
INACTIVE INGREDIENTS: WATER; TROLAMINE; GLYCERIN; PROPYLENE GLYCOL; ALPHA-TOCOPHEROL; ALOE VERA LEAF; CARBOMER HOMOPOLYMER TYPE C

Antibacterial Hand Sanitizer Gel

Active Ingredients Purpose

Ethyl Alcohol 62 percent Antiseptic

PURPOSE

Uses: Hand sanitizer to help decrease bacteria on the skin.

When water, soap and towel are not available.

Recommended for repeated use.

WARNINGS

For external use only.

Flammable. Keep away from fire or flame.

Do not apply around eyes. Do not use in ears and mouth.

When using this product, avoid contact with eyes.

In case of contact flush eyes with water.

Stop use and ask a doctor if redness or irritation develop and persist for more than 72 hours.

Keep out of reach of children. Children must be supervised in use of this product.

DOSAGE AND ADMINISTRATION

Directions: Squirt as needed into your palms and thoroughly spread on both hands. Rub into skin until dry

Other Information: Store at 20 degrees C (68 degrees to 77 degrees F)

May discolor fabrics

INACTIVE INGREDIENT

Inactive Ingredients: water, triethanolamine, glycerin, propylene glycol, Vitamin E, aloe vera gel, carbormer, fragrance

PACKAGE LABEL

Antibacterial Hand Sanitizer Gel

2.0 Fl oz 60(ml)

Made In China